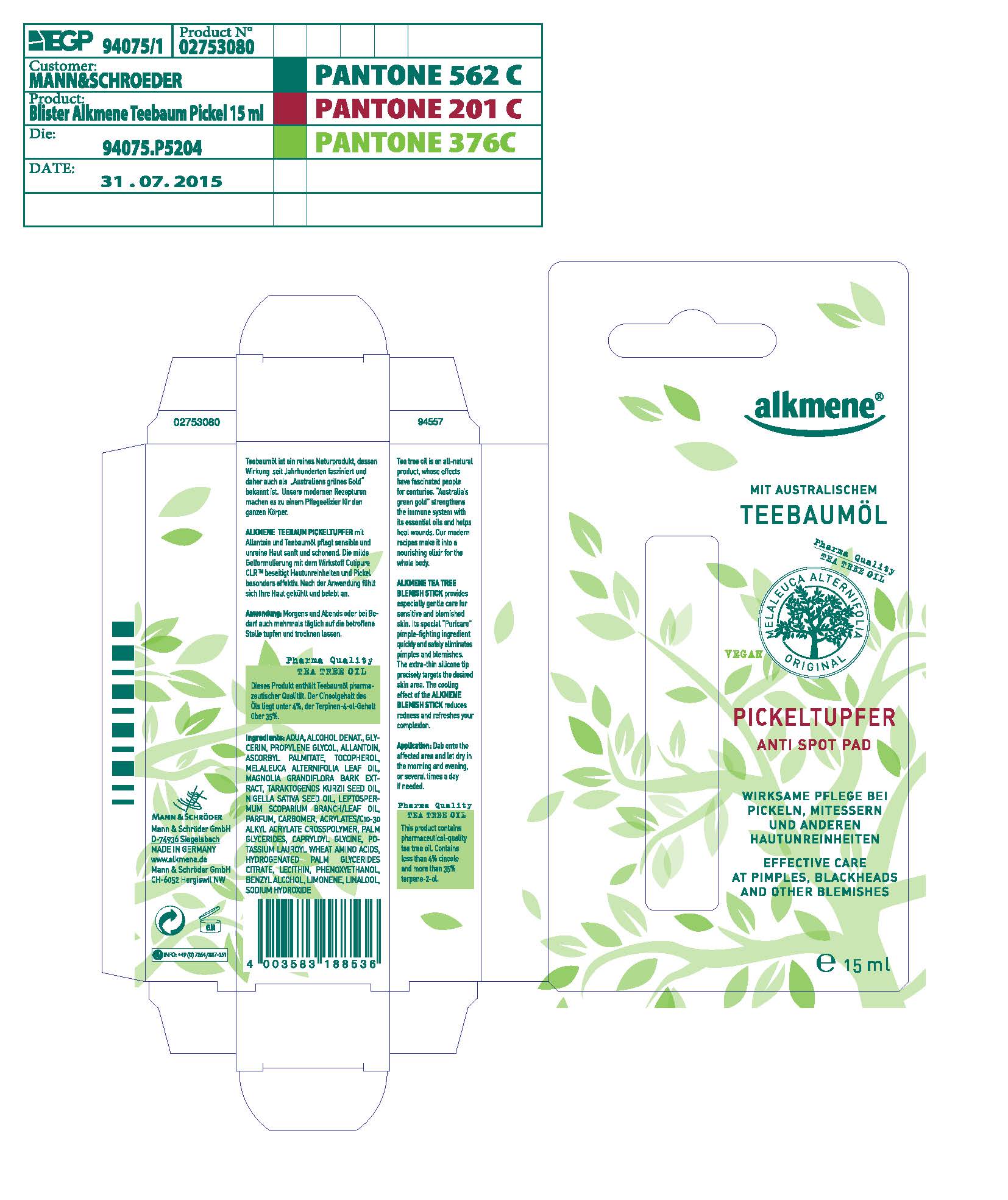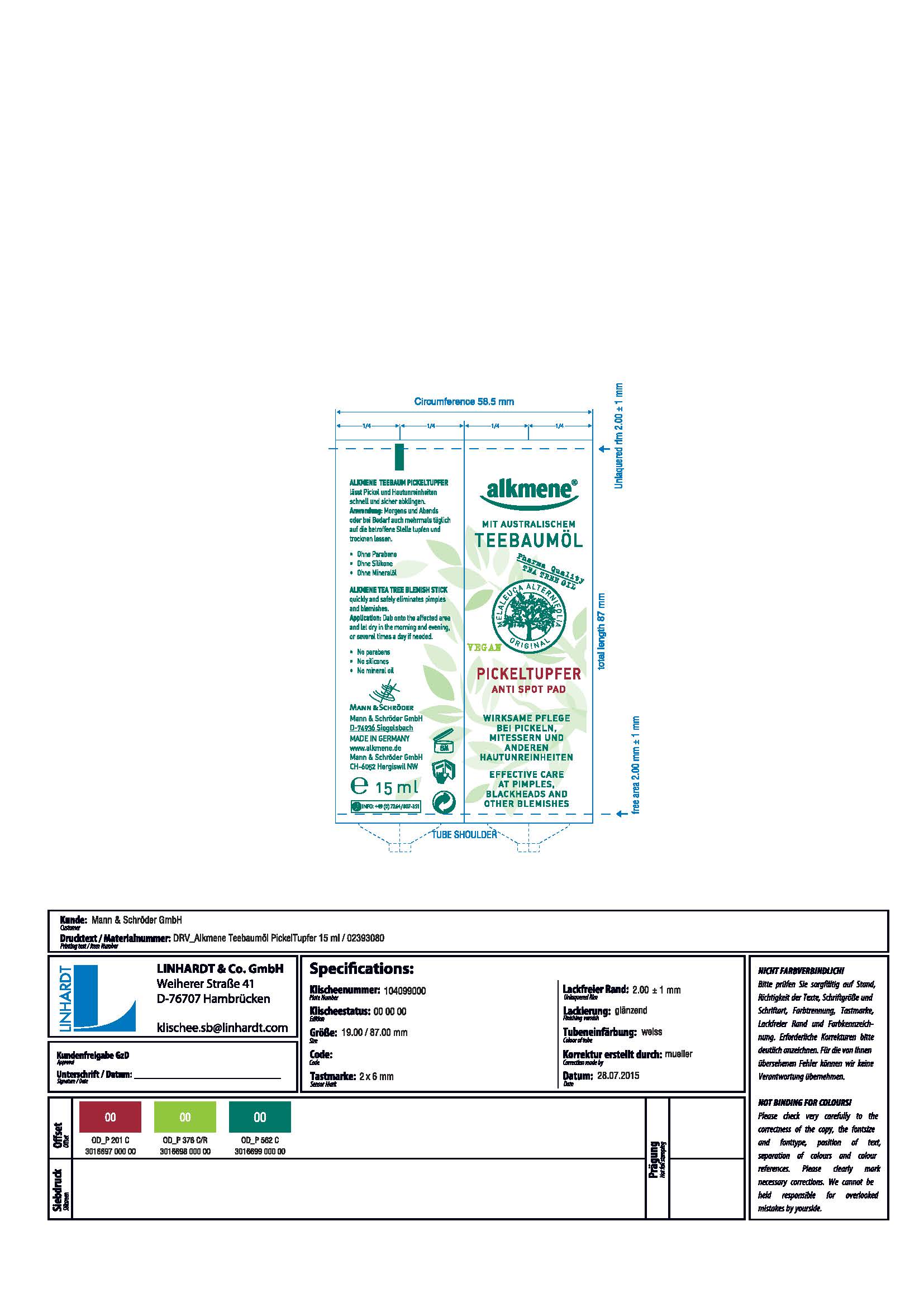 DRUG LABEL: Alkmene Anti Spot pad
NDC: 71084-001 | Form: LIQUID
Manufacturer: Mann & Schroeder GmbH
Category: otc | Type: HUMAN OTC DRUG LABEL
Date: 20170116

ACTIVE INGREDIENTS: TEA TREE OIL 48 g/100 g
INACTIVE INGREDIENTS: WATER; ALCOHOL; ALLANTOIN; GLYCERIN; ASCORBYL PALMITATE; TOCOPHEROL; MANUKA OIL; CARBOMER 934; MAGNOLIA GRANDIFLORA BARK; NIGELLA SATIVA SEED OIL; ACRYLAMIDE; HYDROGENATED PALM GLYCERIDES; POTASSIUM LAURATE; AMINO ACIDS; LECITHIN, SUNFLOWER; PHENOXYETHANOL; .ALPHA.-(.ALPHA.-AMINOPROPYL)BENZYL ALCOHOL; LIMONENE, (+)-; SODIUM HYDROXIDE; LINALOOL, (+/-)-

Purpose -

Provides especially gentle care for sensitive and blemished skin.

It's special puricare pimple-fighting ingredient quickly and safely eliminates pimples and blemishes.

The cooling effect of the Alkemene Blemish stick reduces redness and refreshes your complexion.

ACTIVE INGREDIENT

Tea Tree Oil

DOSAGE AND ADMINISTRATION

Dab onto the affected area and let dry in the morning and evening, or several times a day if needed.

Keep out of reach

INACTIVE INGREDIENT

LINALOOL
ALLANTOIN
GLYCERIN
ASCORBYL PALMITATE
TOCOPHEROL
MANUKA OIL
CARBOMER 934
MAGNOLIA GRANDIFLORA BARK
NIGELLA SATIVA SEED OIL
ACRYLAMIDE
HYDROGENATED PALM GLYCERIDES
AMINO ACIDS
POTASSIUM LAURATE
LECITHIN, SUNFLOWER
PHENOXYETHANOL
BENZYL ALCOHOL
LIMONENE
SODIUM HYDROXIDE
WATER
ALCOHOL

INDICATIONS AND USAGE

Dab onto the affected area and let dry in the morning and evening or serveral times a day.

WARNINGS

For external use.